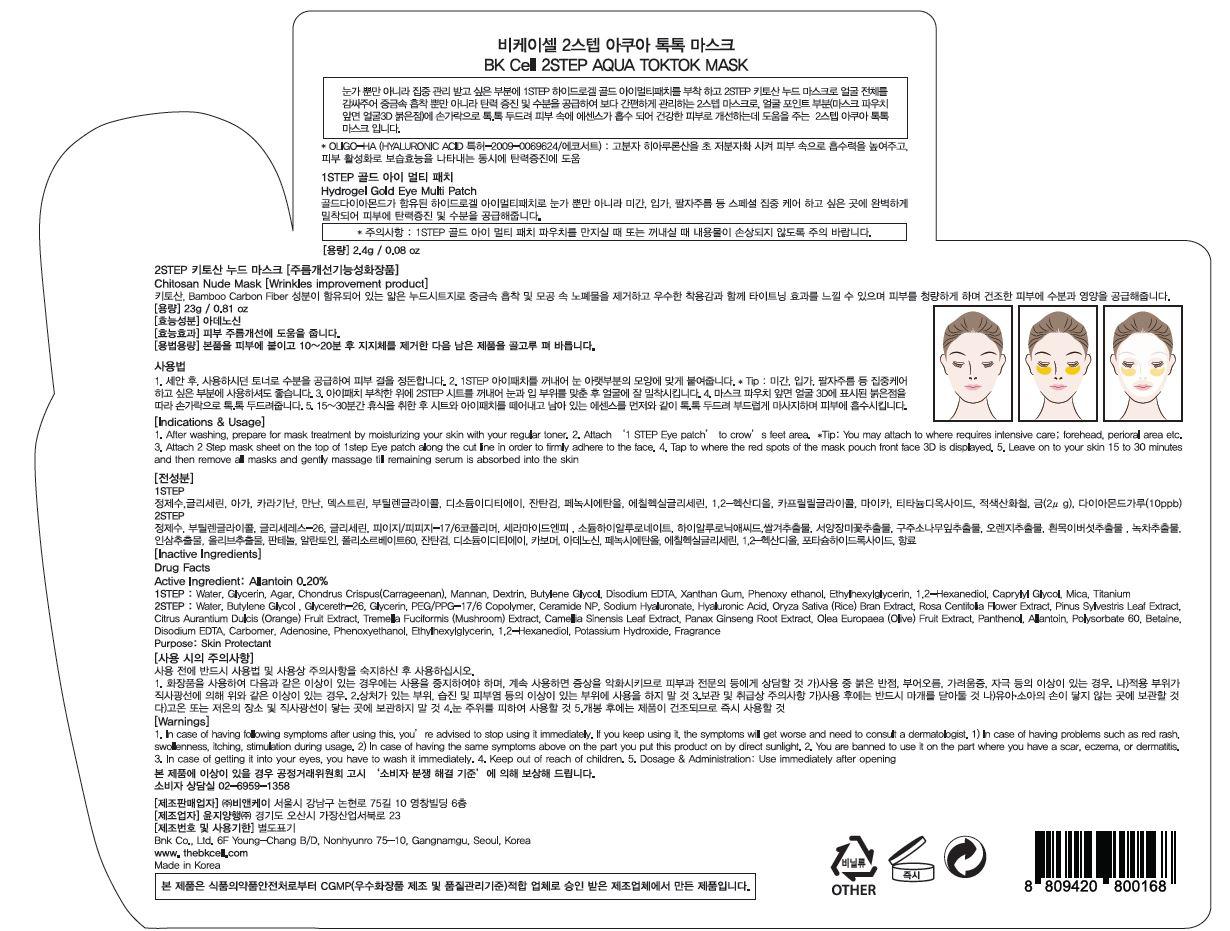 DRUG LABEL: BK Cell 2STEP AQUA TOKTOK MASK
NDC: 69946-070 | Form: PATCH
Manufacturer: BNK CO., LTD.
Category: otc | Type: HUMAN OTC DRUG LABEL
Date: 20150923

ACTIVE INGREDIENTS: Allantoin 0.004 g/2.4 g
INACTIVE INGREDIENTS: Water; Glycerin

ACTIVE INGREDIENT

Active Ingredient: Allantoin 0.20%

INACTIVE INGREDIENT

Inactive Ingredients

ESSENCE: Water, Butylene Glycol, Glycereth-26, Glycerin, PEG/PPG-17/6 Copolymer, Ceramide NP, Sodium Hyaluronate, Hyaluronic Acid, Oryza Sativa (Rice) Bran Extract, Rosa Centifolia Flower Extract, Pinus Sylvestris Leaf Extract, Citrus Aurantium Dulcis (Orange) Fruit Extract, Tremella Fuciformis (Mushroom) Extract, Camellia Sinensis Leaf Extract, Panax Ginseng Root Extract, Olea Europaea (Olive) Fruit Extract, Panthenol, Polysorbate 60, Betaine, Disodium EDTA, Carbomer, Adenosine, Phenoxyethanol, Ethylhexylglycerin, 1,2-Hexanediol, Potassium Hydroxide, Fragrance

EYE GEL: Water, Glycerin, Agar, Chondrus Crispus(Carrageenan), Mannan, Dextrin, Butylene Glycol, Disodium EDTA, Xanthan Gum, Phenoxy ethanol, Ethylhexylglycerin, 1,2-Hexanediol, Caprylyl Glycol, Mica, Titanium Dioxide, Iron Oxides, Gold, Diamond powder

PURPOSE

Purpose: Skin Protectant

WARNINGS

Warnings: 1. In case of having following symptoms after using this, you’re advised to stop using it immediately. If you keep using it, the symptoms will get worse and need to consult a dermatologist. 1) In case of having problems such as red rash, swollenness, itching, stimulation during usage. 2) In case of having the same symptoms above on the part you put this product on by direct sunlight. 2. You are banned to use it on the part where you have a scar, eczema, or dermatitis. 3. In case of getting it into your eyes, you have to wash it immediately.

Keep out of reach of children: Keep out of reach of babies and children

INDICATIONS & USAGE

Indications & Usage: 1. After washing, prepare for mask treatment by moisturizing your skin with your regular toner. 2. Wear the mask, follow the cutting leave the eyes and mouth a space after removing plastic cover slip of the one side and then remove the opposite surface plastic cover slip. 3. Leave the mask 15 to 20 minutes and take it off, Massage and dab the face gently let the essence absorb into skin cell well.

DOSAGE & ADMINISTRATION

Dosage & Administration: Use immediately after opening